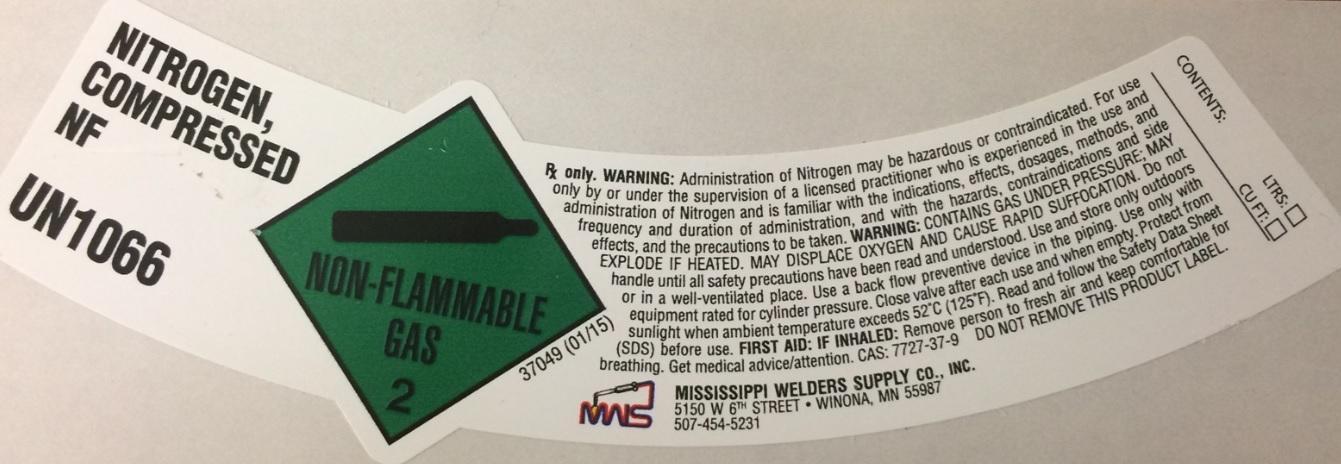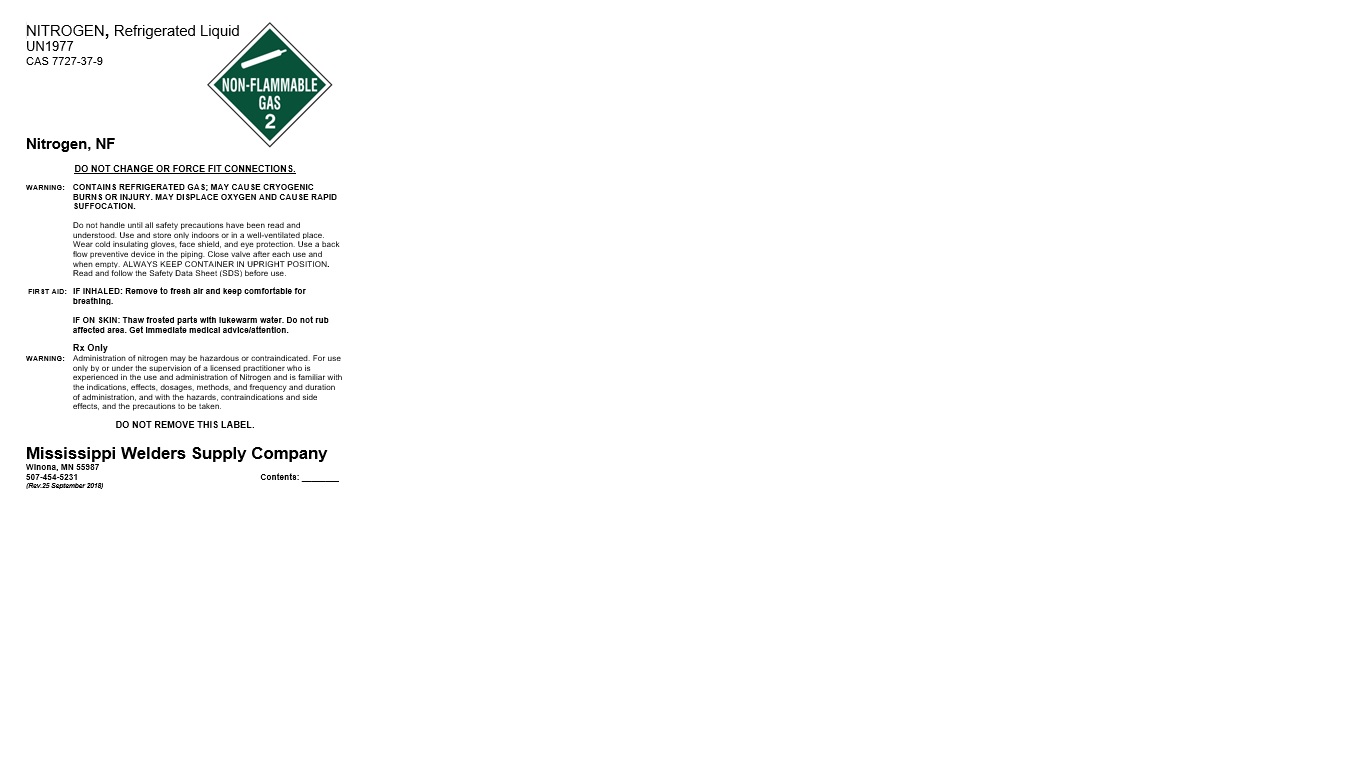 DRUG LABEL: Nitrogen
NDC: 51996-013 | Form: GAS
Manufacturer: Mississippi Welders Supply Company, Inc.
Category: animal | Type: PRESCRIPTION ANIMAL DRUG LABEL
Date: 20251125

ACTIVE INGREDIENTS: Nitrogen 990 mL/1 L

nitrogen

PACKAGE LABEL

NITROGEN, Refrigerated Liquid
UN1977
CAS 7727-37-9

Nitrogen, NF

DO NOT CHANGE OR FORCE FIT CONNECTIONS.

WARNING: CONTAINS REFRIGERATED GAS; MAY CAUSE CRYOGENIC BURNS OR INJURY. MAY DISPLACE OXYGEN AND CAUSE RAPID SUFFOCATION.

Do not handle until all safety precautions have been read and understood. Use and store only indoors or in a well-ventilated place. Wear cold insulating gloves, face shield, and eye protection. Use a back flow preventive device in the piping. Close valve after each use and when empty. ALWAYS KEEP CONTAINER IN UPRIGHT POSITION. Read and follow the Safety Data Sheet (SDS) before use.

FIRST AID: IF INHALED: Remove to fresh air and keep comfortable for breathing.

IF ON SKIN: Thaw frosted parts with lukewarm water. Do not rub affected area. Get immediate medical advice/attention.

Rx Only
WARNING: Administration of nitrogen may be hazardous or contraindicated. For use only by or under the supervision of a licensed practitioner who is experienced in the use and administration of Nitrogen and is familiar with the indications, effects, dosages, methods, and frequency and duration of administration, and with the hazards, contraindications and side effects, and the precautions to be taken.

DO NOT REMOVE THIS LABEL.

Mississippi Welders Supply Company
Winona, MN 55987
507-454-5231 Contents: ________
(Rev.25 September 2018)

PACKAGE LABEL

NITROGEN, COMPRESSED,NF
UN1066

NON-FLAMMABLE GAS 2

Rx only. WARNING: Administration of Nitrogen may be hazardous or contraindicated. For use only by or under the supervision of a licensed practitioner who is experienced in the use and administration of Nitrogen and is familiar with the indications, effects, dosages, methods, and frequency and duration of administration, and with the hazards, contraindications and side effects, and the precautions to be taken. WARNING: CONTAINS GAS UNDER PRESSURE MAY EXPLODE IF HEATED. MAY DISPLACE OXYGEN AND CAUSE RAPID SUFFOCATION. Do not handle until all safety precautions have been read and understood. Use and store only outdoors or in a well-ventilated place. Use a back flow preventive device in the piping. Use only with equipment rated for cylinder pressure. Close valve after each use and when empty. Protect from sunlight when ambient temperature exceeds 52 degrees C (125 degrees F). Read and follow the Safety Data Sheet (SDS) before use. FIRST AID: IF INHALED: Remove person to fresh air and keep comfortable for breathing. Get medical advice/attentions. CAS: 7727-37-9. DO NOT REMOVE THIS PRODUCT LABEL.

MISSISSIPPI WELDERS SUPPLY CO., INC.
5150 W 6TH STREET, WINONA, MN 55987
507-454-5231

CONTENTS: LTRS:
CU. FT.: